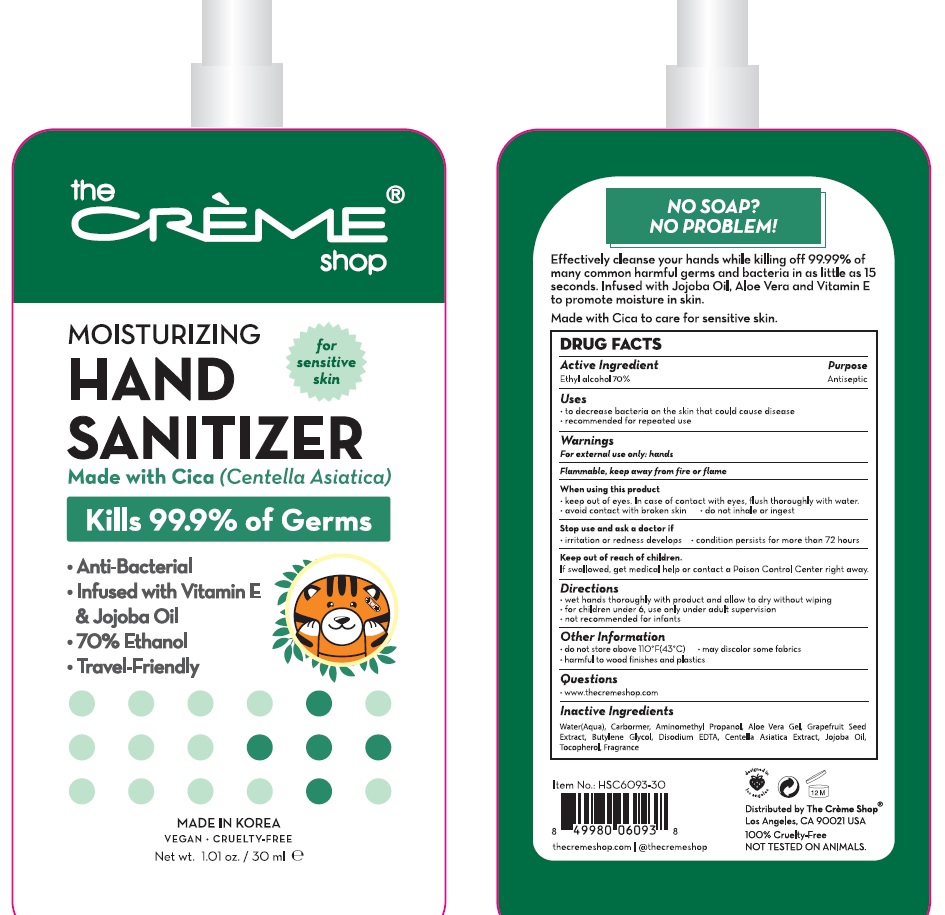 DRUG LABEL: The Creme Shop Cica Hand Sanitizer
NDC: 74923-120 | Form: GEL
Manufacturer: THE SUN CO.LTD
Category: otc | Type: HUMAN OTC DRUG LABEL
Date: 20200701

ACTIVE INGREDIENTS: Alcohol 21 mL/30 mL
INACTIVE INGREDIENTS: Water; CARBOMER HOMOPOLYMER, UNSPECIFIED TYPE; AminomethylPropanol; ALOE VERA LEAF; CITRUS PARADISI SEED; Butylene Glycol; EDETATE DISODIUM ANHYDROUS; CENTELLA ASIATICA WHOLE; Jojoba Oil; TOCOPHEROL

ACTIVE INGREDIENT

Ethyl Alcohol 70.0%

INACTIVE INGREDIENTS

Water(Aqua), Carbomer, Aminomethyl Propanol, Aloe Vera Gel, Grapefruit Seed Extract, Butylene Glycol, Disodium EDTA, Centella Asiatica Extract, Jojoba Oil, Tocopherol, Fragrance

PURPOSE

Antiseptic

WARNINGS

For external use only-hands

Flammable. Keep away from heat and flame.

When using this product ■ Keep out of eyes. In case of contact with eyes,
flush thoroughly with water. ■ Avoid contact with broken skin. ■ Do not inhale or ingest.

Stop use and ask a doctor if
■irritation or redness develops
■condition persists for more than 72 hours

KEEP OUT OF REACH OF CHILDREN

If swallowed, get medical help or contact a Poison Control Center.

Uses

■ to decrease bacteria on the skin that could cause disease
■ recommended for repeated use

Directions

■ wet hands thoroughly with product and allow to dry without wiping
■ For children under 6, use only under adult supervision
■ not recommended for infants

Other Information

■ do not store above 110F(40C)
■ may discolor some fabrics
■ harmful to wood finishes and plastics

QUESTIONS

www thecremeshop.com